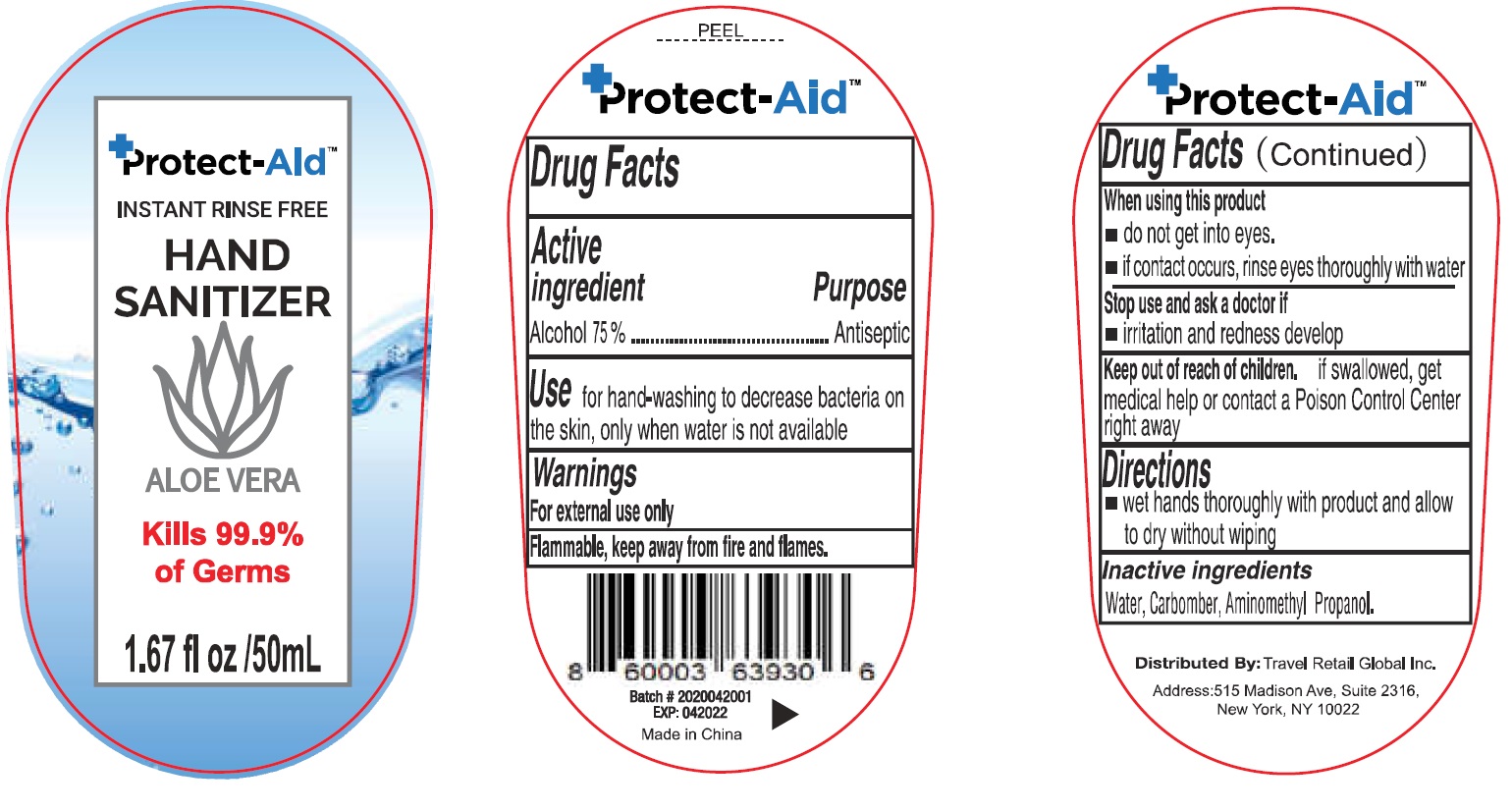 DRUG LABEL: INSTANT FREE HAND SANITIZER
NDC: 77129-000 | Form: GEL
Manufacturer: Travel Retail Global Inc
Category: otc | Type: HUMAN OTC DRUG LABEL
Date: 20231026

ACTIVE INGREDIENTS: ALCOHOL 0.75 mL/1 mL
INACTIVE INGREDIENTS: WATER; CARBOMER HOMOPOLYMER, UNSPECIFIED TYPE; AMINOMETHYLPROPANOL

INSTANT RINSE FREE HAND SANITIZER

Active ingredient

Alcohol 75%

Purpose

Antiseptic

Use

for hand-washing to decrease bacteria on the skin, only when water is not available

Warnings

For external use only

Flammable, keep away from fire and flames.

When using this product

- do not get into eyes.
- if contact occurs, rinse eyes thoroughly with water

Stop use and ask a doctor if

irritation and redness develop

Keep out of reach of children.

if swallowed, get medical help or contact a Poison Control Center right away

Directions

wet hands thoroughly with product and allow to dry without wiping

Inactive ingredients

Water, Carbomer, Aminomethyl Propanol.